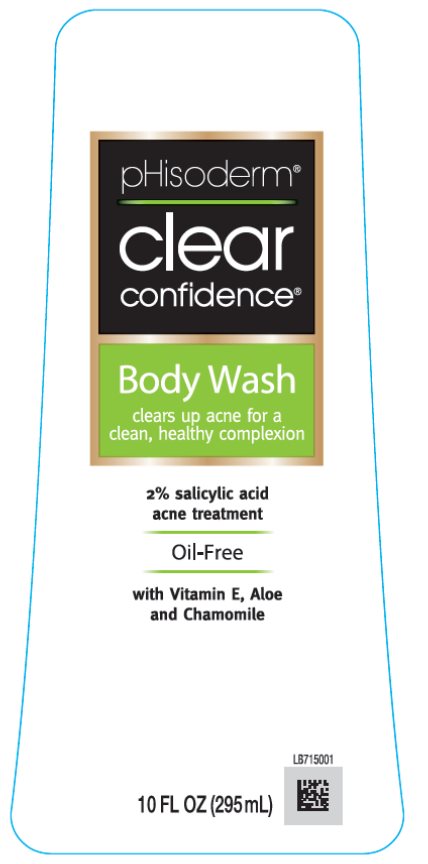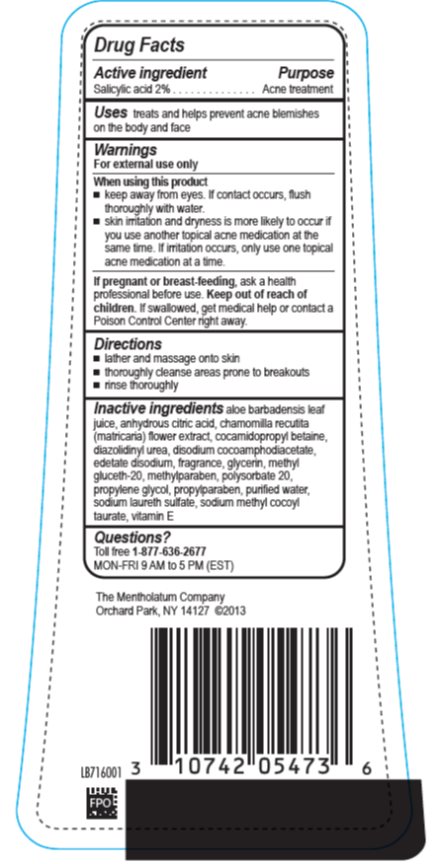 DRUG LABEL: pHisoderm Clear Confidence Body Wash
NDC: 10742-1442 | Form: LIQUID
Manufacturer: The Mentholatum Company
Category: otc | Type: HUMAN OTC DRUG LABEL
Date: 20241213

ACTIVE INGREDIENTS: SALICYLIC ACID 20 mg/1 mL
INACTIVE INGREDIENTS: ALOE VERA LEAF; ANHYDROUS CITRIC ACID; CHAMOMILE; COCAMIDOPROPYL BETAINE; DIAZOLIDINYL UREA; DISODIUM COCOAMPHODIACETATE; EDETATE DISODIUM; GLYCERIN; METHYL GLUCETH-20; METHYLPARABEN; POLYSORBATE 20; PROPYLENE GLYCOL; PROPYLPARABEN; WATER; SODIUM LAURETH-3 SULFATE; SODIUM METHYL COCOYL TAURATE; .ALPHA.-TOCOPHEROL

Drug Facts - pHisoderm Clear Confidence Body Wash

Active ingredient

Salicylic acid 2%

Purpose

Acne treatment

Uses

treats and helps prevent acne blemishes on the body and face

Warnings

For external use only

When using this product

- keep away from eyes. If contact occurs, flush thoroughly with water.
- skin irritation and dryness is more likely to occur if you use another topical acne medication at the same time. If irritation occurs, only use one topical acne medication at a time.

If pregnant or breast-feeding,

ask a health professional before use.

Keep out of reach of children.

If swallowed, get medical help or contact a Poison Control Center right away.

Directions

- lather and massage onto skin
- thoroughly cleanse areas prone to breakouts
- rinse thoroughly

Inactive ingredients

aloe barbadensis leaf juice, anhydrous citric acid, chamomilla recutita (matricaria) flower extract, cocamidopropyl betaine, diazolidinyl urea, disodium cocoamphodiacetate, edetate disodium, fragrance, glycerin, methyl gluceth-20, methylparaben, polysorbate 20, propylene glycol, propylparaben, purified water, sodium laureth sulfate, sodium methyl cocoyl taurate, vitamin E

Questions?

Toll free 1-877-636-2677 MON-FRI 9 AM – 5 PM (EST)